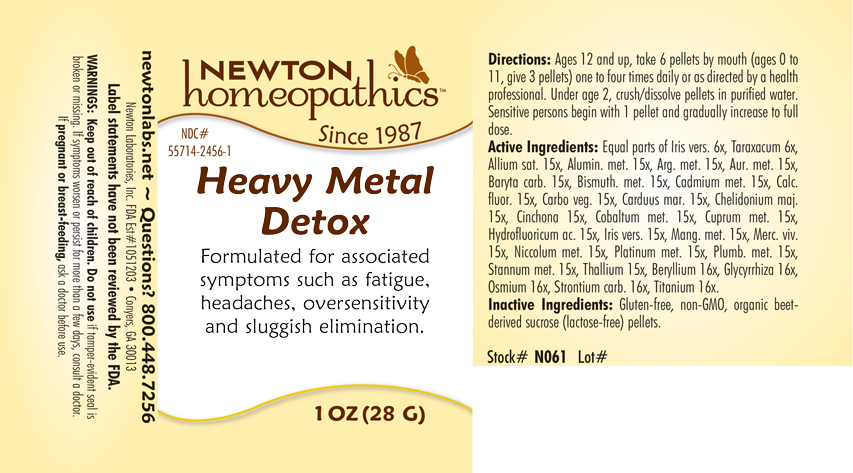 DRUG LABEL: Heavy Metal Detox
NDC: 55714-2456 | Form: PELLET
Manufacturer: Newton Laboratories, Inc.
Category: homeopathic | Type: HUMAN OTC DRUG LABEL
Date: 20250206

ACTIVE INGREDIENTS: GARLIC 15 [hp_X]/1 g; ALUMINUM 15 [hp_X]/1 g; SILVER 15 [hp_X]/1 g; GOLD 15 [hp_X]/1 g; BARIUM CARBONATE 15 [hp_X]/1 g; CALCIUM FLUORIDE 15 [hp_X]/1 g; BERYLLIUM 16 [hp_X]/1 g; BISMUTH 15 [hp_X]/1 g; CADMIUM 15 [hp_X]/1 g; ACTIVATED CHARCOAL 15 [hp_X]/1 g; CHELIDONIUM MAJUS 15 [hp_X]/1 g; CINCHONA OFFICINALIS BARK 15 [hp_X]/1 g; COBALT 15 [hp_X]/1 g; COPPER 15 [hp_X]/1 g; GLYCYRRHIZA GLABRA 16 [hp_X]/1 g; HYDROFLUORIC ACID 15 [hp_X]/1 g; IRIS VERSICOLOR ROOT 15 [hp_X]/1 g; MANGANESE 15 [hp_X]/1 g; MERCURY 15 [hp_X]/1 g; NICKEL 15 [hp_X]/1 g; OSMIUM 16 [hp_X]/1 g; PLATINUM 15 [hp_X]/1 g; LEAD 15 [hp_X]/1 g; TIN 15 [hp_X]/1 g; STRONTIUM CARBONATE 16 [hp_X]/1 g; THALLIUM 15 [hp_X]/1 g; TITANIUM 16 [hp_X]/1 g; MILK THISTLE 15 [hp_X]/1 g; TARAXACUM OFFICINALE 6 [hp_X]/1 g
INACTIVE INGREDIENTS: SUCROSE

Heavy 2456P

INDICATIONS & USAGE SECTION

Formulated for associated symptoms such as fatigue, headaches, oversensitivity and sluggish elimination.

DOSAGE & ADMINISTRATION SECTION

Directions: Ages 12 and up, take 6 pellets by mouth (ages 0 to 11, give 3 pellets) one to four times daily or as directed by a health professional. Under age 2, crush/dissolve pellets in purified water. Sensitive persons begin with 1 pellet and gradually increase to full dose.

OTC - ACTIVE INGREDIENT SECTION

Equal parts of Iris versicolor 6x, Taraxacum officinale 6x, Allium sativum 15x, Aluminium metallicum 15x, Argentum metallicum 15x, Aurum metallicum 15x, Baryta carbonica 15x, Bismuthum metallicum 15x, Cadmium metallicum 15x, Calcarea fluorica 15x, Carbo vegetabilis 15x, Carduus marianus 15x Chelidonium majus 15x, Cinchona officinalis 15x, Cobaltum metallicum 15x, Cuprum metallicum 15x, Hydrofluoricum acidum 15x, Iris versicolor 15x, Manganum metallicum 15x, Mercurius vivus 15x, Niccolum metallicum 15x, Platinum metallicum 15x, Plumbum metallicum 15x, Stannum metallicum 15x, Thallium metallicum 15x, Beryllium metallicum 16x, Glycyrrhiza glabra 16x, Osmium metallicum 16x, Strontium carbonicum 16x, Titanium metallicum 16x.

OTC - PURPOSE SECTION

Formulated for associated symptoms such as fatigue, headaches, oversensitivity and sluggish elimination.

INACTIVE INGREDIENT SECTION

Inactive Ingredients: Gluten-free, non-GMO, organic beet-derived sucrose (lactose-free) pellets.

QUESTIONS SECTION

newtonlabs.net – Questions? 800.448.7256

Newton Laboratories, Inc. FDA Est # 1051203 - Conyers, GA 30013

WARNINGS SECTION

WARNINGS: Keep out of reach of children. Do not use if tamper-evident seal is broken or missing. If symptoms worsen or persist for more than a few days, consult a doctor. If pregnant or breast-feeding, ask a doctor before use.

OTC - PREGNANCY OR BREAST FEEDING SECTION

If pregnant or breast-feeding, ask a doctor before use.

OTC - KEEP OUT OF REACH OF CHILDREN SECTION

Keep out of reach of children.